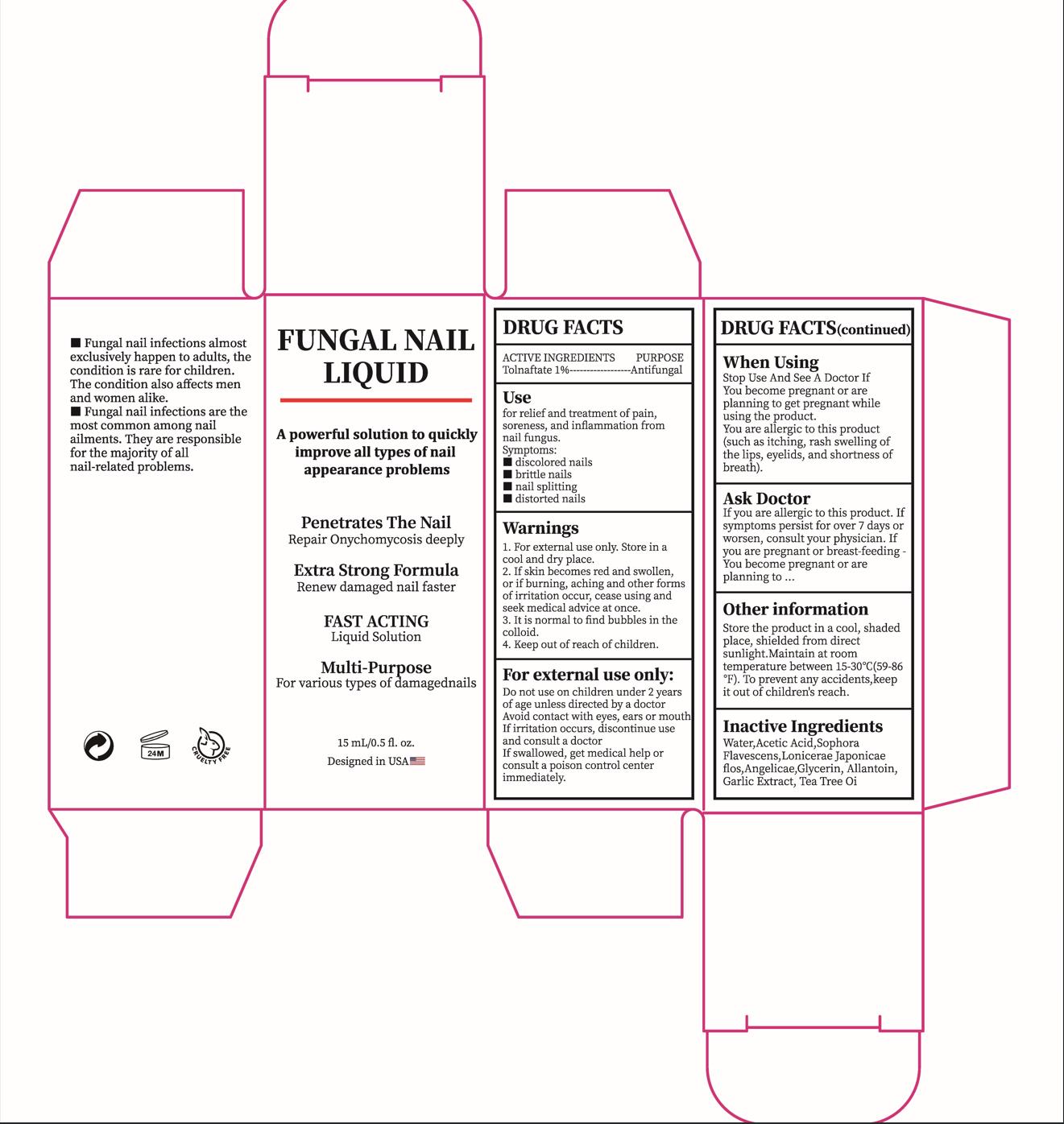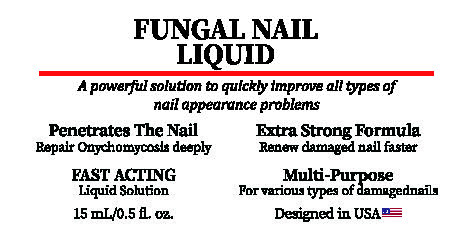 DRUG LABEL: Fungal Nail Liquid
NDC: 84023-501 | Form: LIQUID
Manufacturer: Shenzhen Yangan Technology Co., Ltd.
Category: otc | Type: HUMAN OTC DRUG LABEL
Date: 20240308

ACTIVE INGREDIENTS: TOLNAFTATE 1 g/100 mL
INACTIVE INGREDIENTS: ACETIC ACID; SOPHORA FLAVESCENS ROOT; LONICERA JAPONICA FLOWER; ANGELICA ACUTILOBA ROOT; WATER; GLYCERIN; ALLANTOIN; GARLIC; TEA TREE OIL

FUNGAL NAIL LIQUID

FUNGAL NAIL LIQUID

ACTIVE INGREDIENT

Tolnaftate 1%

PURPOSE

Antifungal

INDICATIONS AND USAGE

for relief and treatment of pain,soreness,and inflammation from nail fungus.
Symptoms:
discolored nails
brittle nails
nail splitting
distorted nails

WARNINGS

For external use only

Stop Use And See A Doctor IfYou become pregnant or areplanning to get pregnant whileusing the product.You are allergic to this product(such as itching, rash swelling ofthe lips, eyelids, and shortness ofbreath).

When Using
Stop Use And See A Doctor IfYou become pregnant or areplanning to get pregnant whileusing the product.You are allergic to this product(such as itching, rash swelling ofthe lips, eyelids, and shortness ofbreath).

STOP USE

If skin becomes red and swollen, or if burning, aching and other forms ofirritation occur, cease using and seek medical advice at once.

If you are allergic to this product. Ifsymptoms persist for over 7 days orworsen, consult your physician.Ifyou are pregnant or breast-feeding You become pregnant or areplanning to

Keep out of reach of children.

Do not use on children under 2 yearsof age unless directed by a doctorAvoid contact with eyes, ears or mouthIf irritation occurs, discontinue useand consult a doctorIf swallowed, get medical help orconsult a poison control centerimmediately

STORAGE AND HANDLING

Store in a cool and dry place.

INACTIVE INGREDIENT

Water
Acetic Acid
Sophora Flavescens
Lonicerae Japonicae flos
Angelicae
Glycerin
Allantoin
Garlic Extract
Tea Tree Oi